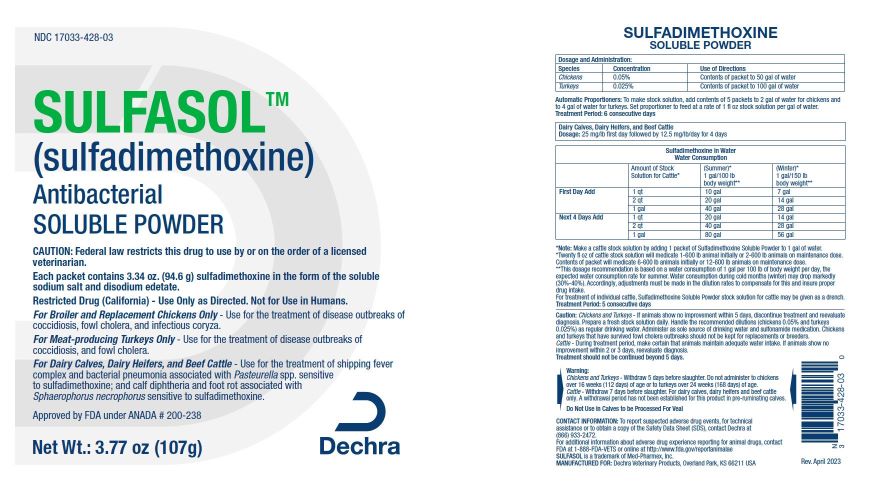 DRUG LABEL: SULFASOL 
NDC: 17033-428 | Form: POWDER, FOR SOLUTION
Manufacturer: Dechra Veterinary Products
Category: animal | Type: PRESCRIPTION ANIMAL DRUG LABEL
Date: 20230517

ACTIVE INGREDIENTS: SULFADIMETHOXINE SODIUM 94.6 g/107 g

SULFASOL SOLUBLE POWDER

DESCRIPTION

(Brand of Sulfadimethoxine)

Antibacterial

CAUTION: Federal (USA) law restricts this drug to use by or on the order of a licensed veterinarian.

Approved by FDA under ANADA #200-238

Restricted Drug (California) - Use Only as Directed. Not for Human Use.

Net Wt.: 3.77 oz (107g)

Each packet contains 3.34 oz. (94.6 g) sulfadimethoxine in the form of the soluble sodium salt and disodium edetate.

INDICATIONS FOR USE:

For Broiler and Replacement Chickens Only - Use for the treatment of disease outbreaks of coccidiosis, fowl cholera, and infectious coryza.

For Meat-producing Turkeys Only - Use for the treatment of disease outbreaks of coccidiosis, and fowl cholera.

For Dairy Calves, Dairy Heifers, and Beef Cattle - Use for the treatment of shipping fever complex and bacterial pneumonia associated with Pasteurella spp. sensitive to sulfadimethoxine; and calf diphtheria and foot rot associated with Sphaerophorus necrophorus sensitive to sulfadimethoxine.

DOSAGE AND ADMINISTRATION

 |  |  |  | SULFADIMETHOXINE
 |  |  |  | SOLUBLE POWDER
Dosage and Administration:
Species |  | Concentration |  |  |  | Use of Directions
Chickens |  | 0.050% |  |  |  | Contents of packet to 50 gal of water
Turkeys |  | 0.025% |  |  |  | Contents of packet to 100 gal of water
Automatic Proportioners: To make stock solution, add contents of 5 packets to 2 gal of water for chickens and to 4 gal of water for turkeys. Set proportioner to feed at a rate of 1 fl oz stock solution per gal of water.
Treatment Period: 6 consecutive days
Dairy Calves, Dairy Heifers, and Beef Cattle
Dosage: 25 mg/lb first day followed by 12.5 mg/lb/day for 4 days
 |  |  |  |  | Sulfadimethoxine in Water
 |  |  |  |  | Water Consumption
 | Amount of Stock Solution; for Cattle* |  |  |  | (Summer)*; 1 gal/100 lb body weight** |  | (Winter)*; 1 gal/150 lb body weight**
First Day Add | 1 qt |  | 10 gal |  |  |  | 7 gal
First Day Add | 2 qt |  | 20 gal |  |  |  | 14 gal
First Day Add | 1 gal |  | 40 gal |  |  |  | 28 gal
Next 4 Days Add | 1 qt |  | 20 gal |  |  |  | 14 gal
Next 4 Days Add | 2 qt |  | 40 gal |  |  |  | 28 gal
Next 4 Days Add | 1 gal |  | 80 gal |  |  |  | 56 gal
*Note: Make a cattle stock solution by adding 1 packet of Sulfadimethoxine Soluble Powder to 1 gal of water.
*Twenty fl oz of cattle stock solution will medicate 1-600 lb animal initially or 2-600 lb animals on maintenance dose. Contents of packet will medicate 6-600 lb animals initially or 12-600 lb animals on maintenance dose.
**This dosage recommendation is based on a water consumption of 1 gal per 100 lb of body weight per day, the expected water consumption rate for summer. Water consumption during cold months (winter) may drop markedly (30%-40%). Accordingly, adjustments must be made in the dilution rates to compensate for this and insure proper drug intake.
For treatment of individual cattle, Sulfadimethoxine Soluble Powder stock solution for cattle may be given as a drench.
Treatment Period: 5 consecutive days

WARNINGS AND PRECAUTIONS

CAUTION:

Chickens and Turkeys - If animals show no improvement within 5 days, discontinue treatment and reevaluate diagnosis. Prepare a fresh stock solution daily. Handle the recommended dilutions (chickens 0.05% and turkeys 0.025%) as regular drinking water. Administer as sole source of drinking water and sulfonamide medication. Chickens and turkeys that have survived fowl cholera outbreaks should not be kept for replacements or breeders.

Cattle - During treatment period, make certain that animals maintain adequate water intake. If animals show no improvement within 2 or 3 days, reevaluate diagnosis. Treatment should not be continued beyond 5 days.

WARNINGS:
Chickens and Turkeys - Withdraw 5 days before slaughter. Do not administer to chickens over 16 weeks (112 days) of age or to turkeys over 24 weeks (168 days) of age.

Cattle - Withdraw 7 days before slaughter. For dairy calves, dairy heifers and beef cattle only.

A withdrawal period has not been established for this product in pre-ruminating calves.

Do Not Use in Calves to be Processed For Veal

GENERAL PRECAUTIONS

CONTACT INFORMATION: To report suspected adverse drug events, for technical assistance or to obtain a copy of the Safety Data Sheet (SDS), contact Dechra at (866) 933-2472. For additional information about adverse drug experience reporting for animal drugs, contact FDA at 1-888-FDA-VETS or online at http://www.fda.gov/reportanimalae

SULFASOL is a trademark of Med-Pharmex, Inc.

Manufactured for:
Dechra Veterinary Products, LLC
Overland Park, KS 66211

Rev. 05/2023